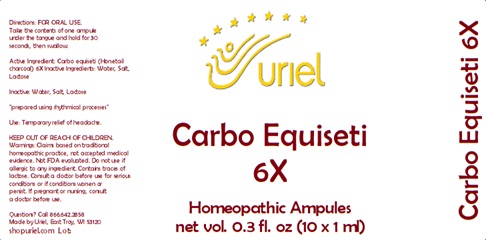 DRUG LABEL: Carbo Equiseti 6X
NDC: 48951-3265 | Form: LIQUID
Manufacturer: Uriel Pharmacy Inc.
Category: homeopathic | Type: HUMAN OTC DRUG LABEL
Date: 20240417

ACTIVE INGREDIENTS: ACTIVATED CHARCOAL 6 [hp_X]/1 mL
INACTIVE INGREDIENTS: WATER; SODIUM CHLORIDE; LACTOSE

Carbo Equiseti 6X

INDICATIONS AND USAGE

Directions: FOR ORAL USE.

DOSAGE AND ADMINISTRATION

Take the contents of one ampule under the tongue and hold for 30 seconds, then swallow.

Active Ingredient: Carbo equiseti (Horsetail charcoal) 6X

Inactive Ingredients: Water, Salt, Lactose

"prepared using rhythmical processes"

PURPOSE

Use: Temporary relief of headache.

KEEP OUT OF REACH OF CHILDREN.

WARNINGS

Warnings: Claims based on traditional homeopathic practice, not accepted medical evidence. Not FDA evaluated. Do not use if allergic to any ingredient. Contains traces of lactose. Consult a doctor before use for serious conditions or if conditions worsen or
persist. If pregnant or nursing, consult a doctor before use.

QUESTIONS

Questions? Call 866.642.2858 Made by Uriel, East Troy, WI 53120 shopuriel.com Lot: